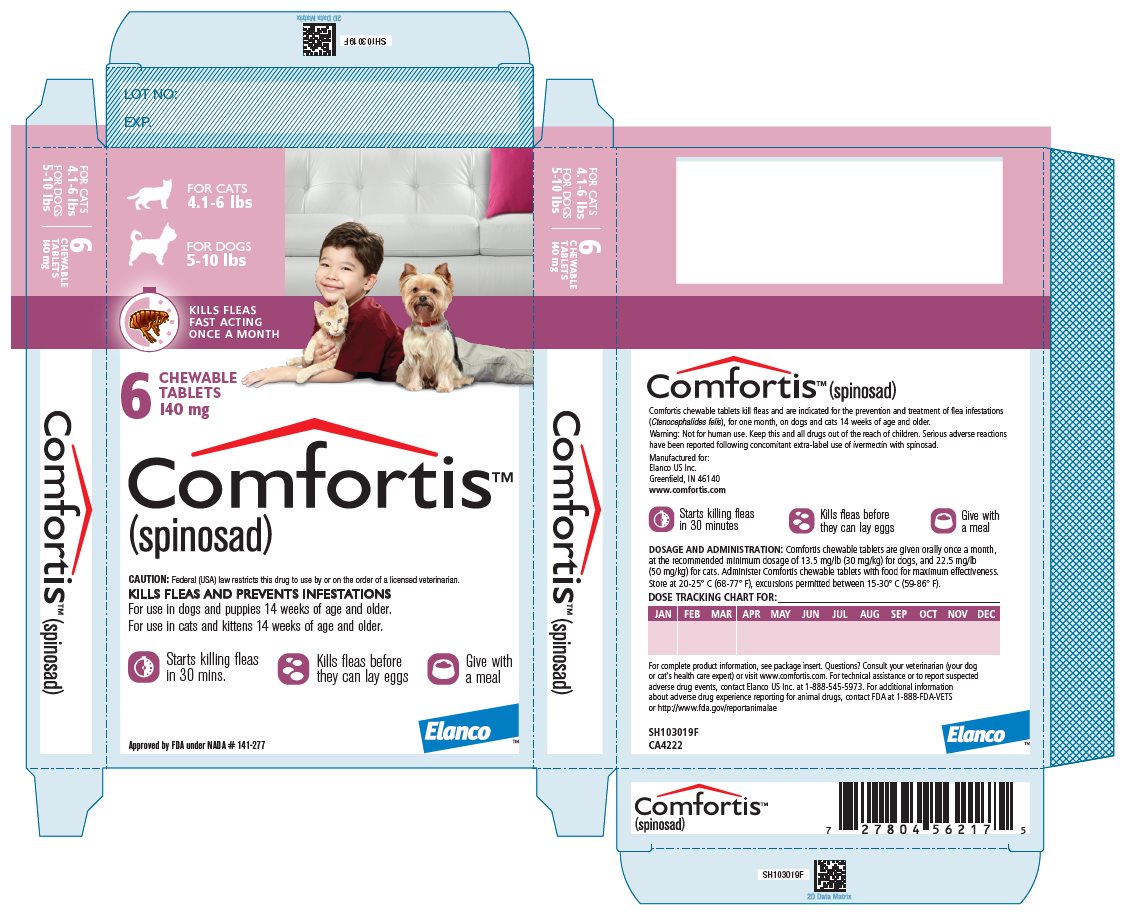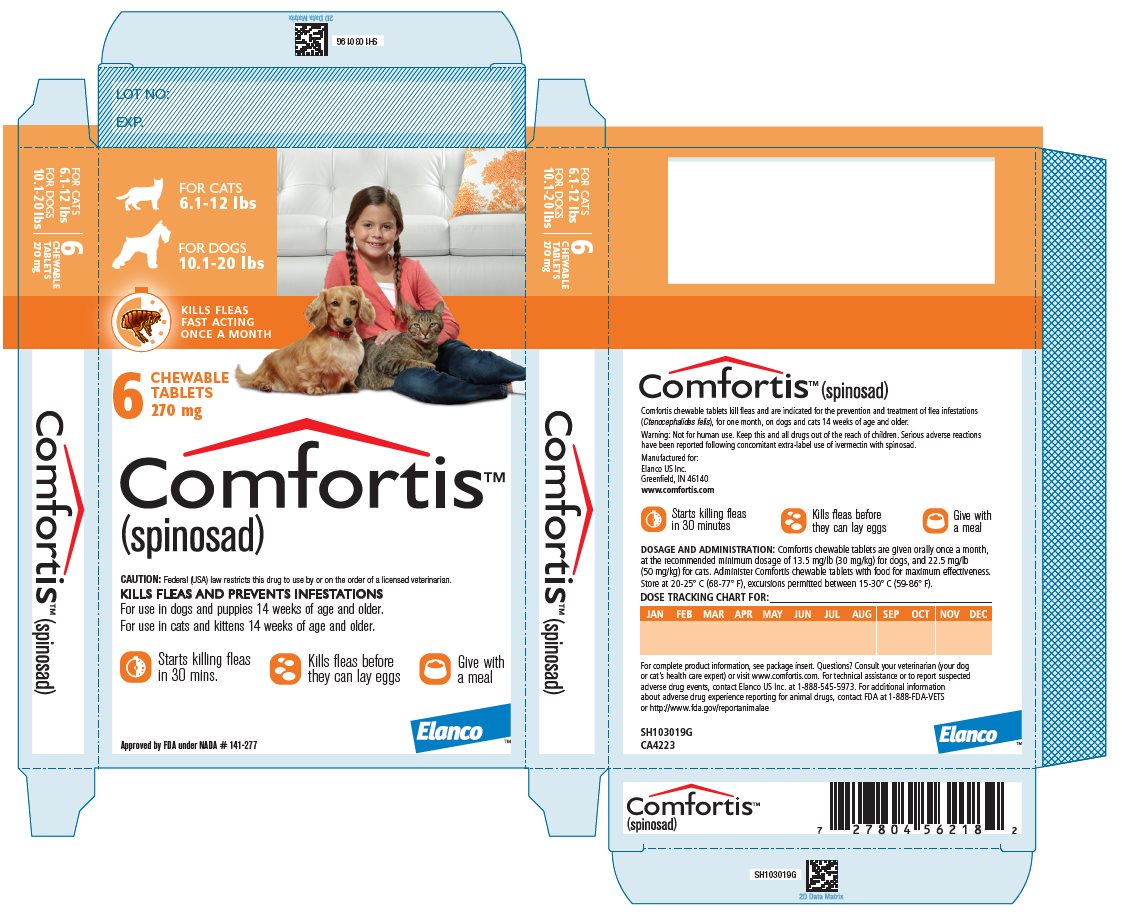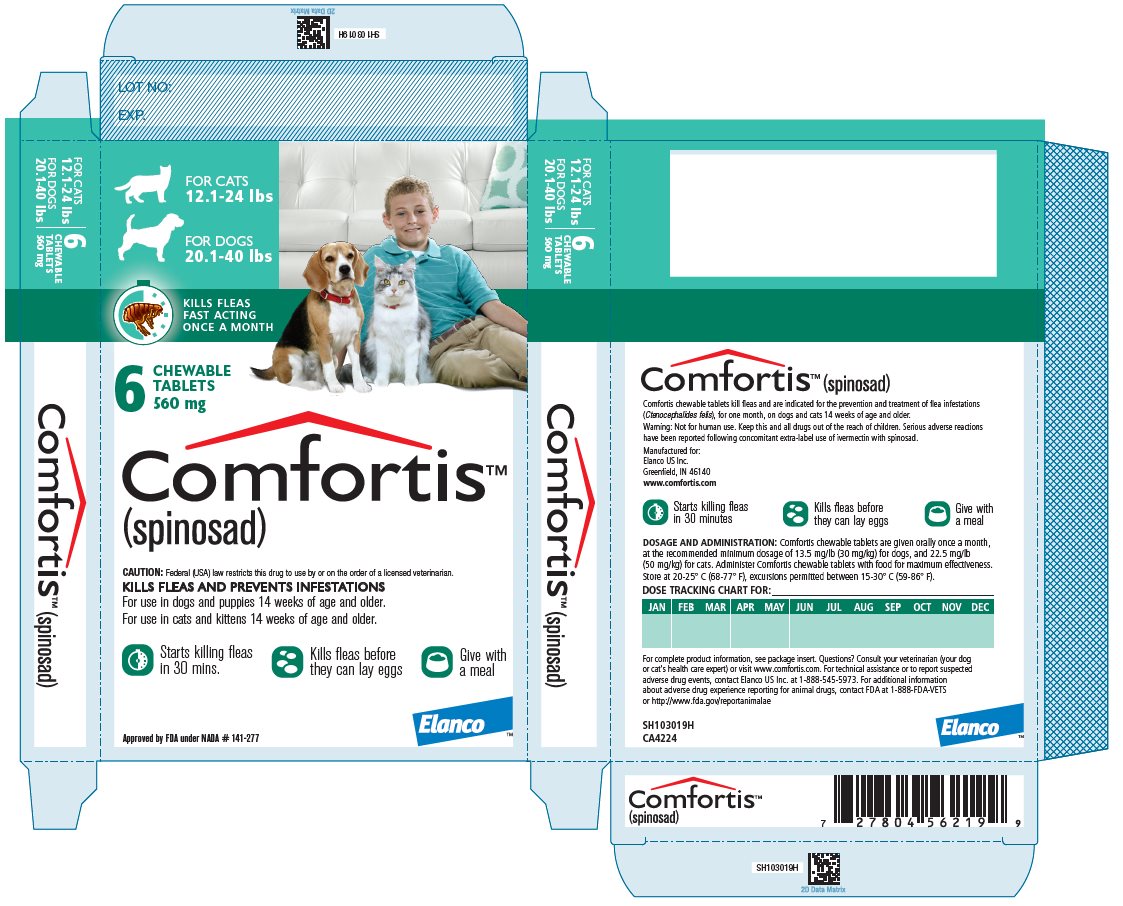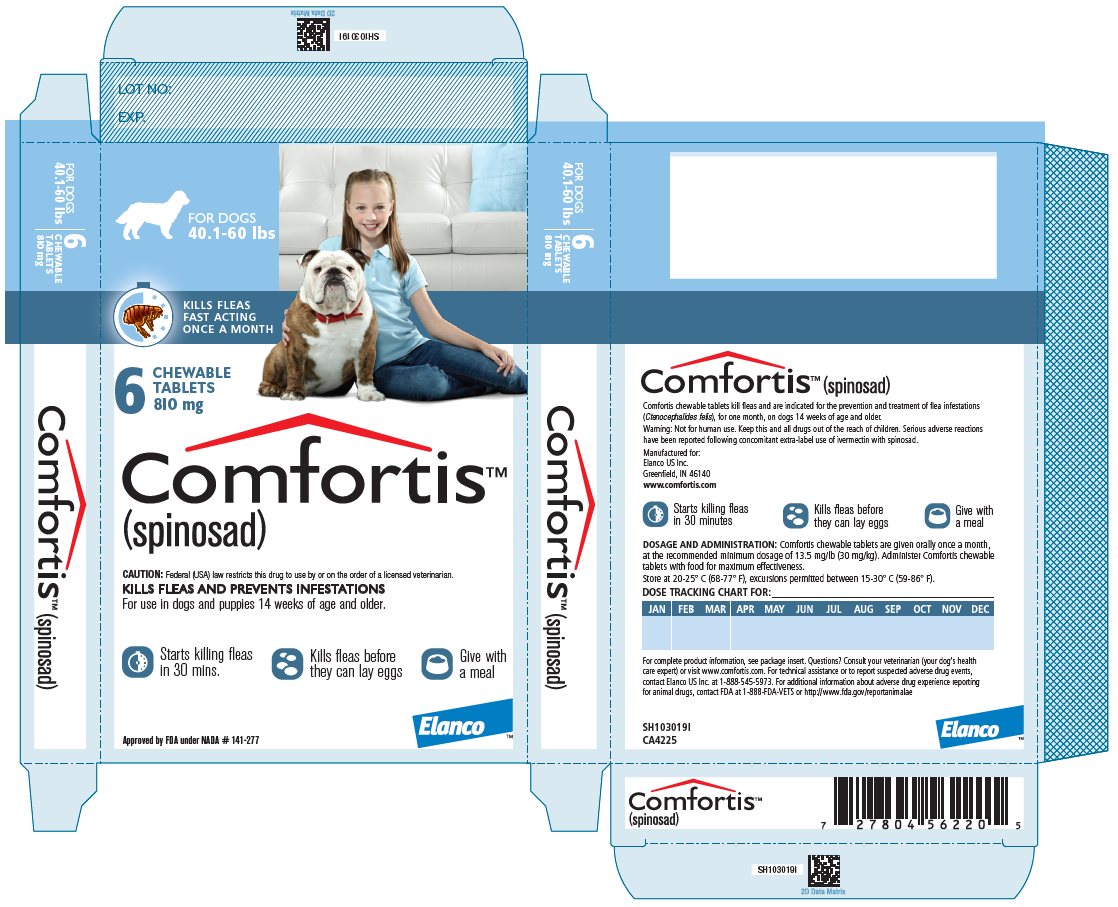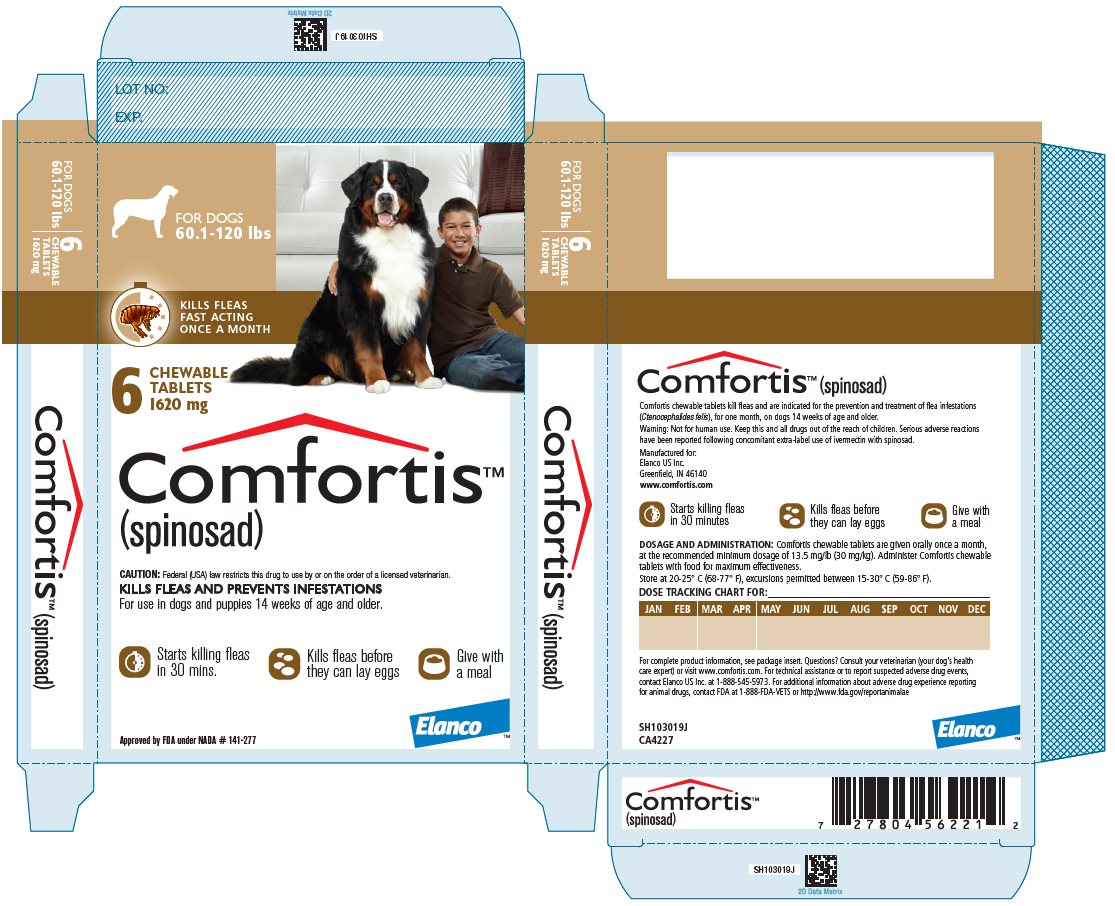 DRUG LABEL: Comfortis
NDC: 58198-0071 | Form: TABLET, CHEWABLE
Manufacturer: Elanco US Inc.
Category: animal | Type: PRESCRIPTION ANIMAL DRUG LABEL
Date: 20241106

ACTIVE INGREDIENTS: Spinosad 140 mg/1 1

Comfortis™
(spinosad)

Chewable Tablets

Comfortis™ Cats
(spinosad)

Chewable Tablets

Caution: Federal law restricts this drug to use by or on the order of a licensed veterinarian.

Description:

COMFORTIS (spinosad) is available in three sizes of chewable flavored tablets for oral administration to cats and kittens according to their weight. Each chewable flavored tablet is formulated to provide a minimum spinosad dosage of 22.5 mg/lb (50 mg/kg). Spinosad is a member of the spinosyns class of insecticides, which are non-antibacterial tetracyclic macrolides. Spinosad contains two major factors, spinosyn A and spinosyn D, derived from the naturally occurring bacterium, Saccharopolyspora spinosa. Spinosyn A and spinosyn D have the chemical compositions 2-[(6-deoxy-2,3,4-tri-O-methyl-α-L-mannopyranosyl)oxy]-13-[[5-(dimethylamino)tetrahydro-6-methyl-2H-pyran-2-yl]oxy]-9-ethyl-2,3,3a,5a,5b,6,9,10,11,12,13,14,16a,16b-tetradecahydro-14-methyl-1H-as-indaceno[3,2-d]oxacyclododecin-7,15-dione and 2-[(6-deoxy-2,3,4-tri-O-methyl-α-L-mannopyranosyl)oxy]-13-[[5-(dimethylamino)tetrahydro-6-methyl-2H-pyran-2-yl]oxy]-9-ethyl-2,3,3a,5a,5b,6,9,10,11,12,13,14,16a,16b-tetradecahydro-4,14-dimethyl-1H-as-indaceno[3,2-d]oxacyclododecin-7,15-dione, respectively.

Indications:

COMFORTIS kills fleas and is indicated for the prevention and treatment of flea infestations (Ctenocephalides felis), for one month, on cats and kittens 14 weeks of age and older and 4.1 pounds of body weight or greater.

Dosage and Administration:

COMFORTIS is given orally once a month, at the minimum dosage of 22.5 mg/lb (50 mg/kg).

Do not use the dosing schedule below when administering COMFORTIS to dogs, as it can result in an overdosage.

Dosage Schedule for Cats:

Body Weight of Cat | Spinosad Per Tablet (mg) | Tablets Administered
4.1 to 6 lbs | 140 | One
6.1 to 12 lbs | 270 | One
12.1 to 24* lbs | 560 | One
*Cats over 24 lbs should be administered the appropriate combination of tablets.

Administer COMFORTIS with food for maximum effectiveness.

COMFORTIS is a chewable tablet that can be consumed by cats when offered by the owner just prior to or after feeding. Alternatively, COMFORTIS may be offered in food or administered like other tablet medications.
COMFORTIS should be administered at monthly intervals.

If vomiting occurs within an hour of administration, redose with another full dose. If a dose is missed, administer COMFORTIS with food and resume a monthly dosing schedule.

Treatment with COMFORTIS may begin at any time of the year, preferably starting one month before fleas become active and continuing monthly through the end of flea season. In areas where fleas are common year-round, monthly treatment with COMFORTIS should continue the entire year without interruption.

To minimize the likelihood of flea reinfestations, it is important to treat all animals within a household with an approved flea protection product.

Contraindications:

There are no known contraindications for the use of COMFORTIS.

WARNINGS:

Not for human use. Keep this and all drugs out of the reach of children.

Keep COMFORTIS in a secure location out of reach of dogs, cats, and other animals to prevent accidental ingestion or overdose.

Precautions:

Use with caution with concomitant extra-label use of ivermectin (see Adverse Reactions and Post-Approval Experience).

The safe use of COMFORTIS in breeding, pregnant, or lactating cats has not been evaluated.

Adverse Reactions:

In a well-controlled US field study, which included a total of 211 cats (139 treated with COMFORTIS and 72 treated with an active topical control once a month for 3 treatments), no serious adverse reactions were attributed to the administration of COMFORTIS.

Over the 90-day study period, all observations of potential adverse reactions were recorded. Reactions that occurred at an incidence > 1% within any of the 3 months of observations are presented in the following table. The most frequently reported adverse reaction in cats was vomiting.

Percentage of Cats (%) with Adverse Reactions

 | Month 1 |  | Month 2 |  | Month 3
 | COMFORTIS (n=139) | Active Topical Control (n=72) | COMFORTIS (n=135) | Active Topical Control (n=69) | COMFORTIS (n=132) | Active Topical Control (n=67)
Vomiting | 14.4 | 1.4 | 14.8 | 1.4 | 13.6 | 4.5
Lethargy | 3.6 | 0.0 | 0.7 | 0.0 | 1.5 | 1.5
Anorexia | 2.2 | 0.0 | 0.7 | 0.0 | 2.3 | 1.5
Weight Loss | 1.4 | 0.0 | 0.0 | 0.0 | 3.0 | 0.0
Diarrhea | 1.4 | 1.4 | 0.7 | 2.9 | 2.3 | 1.5

Over the 3-month (3-dose) study, vomiting occurred on the day of or the day after at least one dose in 28.1% (39/139) of the cats treated with COMFORTIS and in 2.8% (2/72) of the cats treated with the active topical control. Three of the 139 cats treated with COMFORTIS vomited on the day of or the day after all three doses.

Two cats that received extra-label topical otic ivermectin on Day -1 of the field study developed lethargy on Day 1 after COMFORTIS administration on Day 0.

Post-Approval Experience (2023)

The following adverse events are based on post-approval adverse drug experience reporting for COMFORTIS. Not all adverse events are reported to FDA/CVM. It is not always possible to reliably estimate the adverse event frequency or establish a causal relationship to product exposure using these data.

The following adverse events reported for cats are listed in decreasing order of reporting frequency: Vomiting, depression/lethargy, anorexia, behavioral changes, pruritus, diarrhea, ataxia, hyperactivity, hypersalivation, panting, vocalization, dyspnea, twitching, and seizures.

In some cases, death has been reported. Some of these reports involved cats with cardiac disease, including cats with previously undiagnosed cardiac disease.

Following concomitant extra-label use of ivermectin with COMFORTIS, some cats have experienced the following clinical signs: ataxia, trembling/twitching, seizures, mydriasis, disorientation, and transient blindness.

Post-approval experience continues to support the safety of COMFORTIS when used concurrently with heartworm preventatives according to label directions.

Contact Information:

For technical assistance or to report suspected adverse drug experiences, contact Elanco US Inc. at 1-888-545-5973.

For additional information about reporting adverse drug experiences for animal drugs, contact FDA at 1-888-FDA-VETS or http://www.fda.gov/reportanimalae

Mode of Action:

The primary target of action of COMFORTIS in insects is an activation of nicotinic acetylcholine receptors (nAChRs).

Spinosad does not interact with known binding sites of other nicotinic or GABAergic insecticides such as neonicotinides, fiproles, milbemycins, avermectins, and cyclodienes. Insects treated with spinosad show involuntary muscle contractions and tremors resulting from activation of motor neurons. Prolonged spinosad-induced hyperexcitation results in prostration, paralysis, and flea death. The selective toxicity of spinosad between insects and vertebrates may be conferred by the differential sensitivity of the insect versus vertebrate nAChRs.

Effectiveness:

In a well-controlled laboratory study, COMFORTIS began to kill fleas 30 minutes after administration and demonstrated 98% effectiveness within 4 hours. COMFORTIS kills fleas before they can lay eggs. In a separate well-controlled laboratory study, COMFORTIS demonstrated 100% effectiveness on the first day following treatment and >90% effectiveness on Day 30.

If a severe environmental infestation exists, fleas may persist for a period of time after dose administration due to the emergence of adult fleas from pupae already in the environment.

In a field study conducted in households with existing flea infestations, flea count reductions of 97.5% were observed one month after the first treatment and 99.3% after three monthly treatments with COMFORTIS.

Cats with pre-existing signs of flea allergy dermatitis showed improvement in erythema, papules, scaling, alopecia, dermatitis/pyodermatitis, and pruritus as a direct result of eliminating the fleas.

Animal Safety:

In a margin of safety study, COMFORTIS was administered orally to 14-week-old kittens at 1X, 3X, and 5X the upper half (75 – 100 mg/kg) of the therapeutic dose band for six monthly dosing intervals 28 days apart.

Vomiting was observed across all groups, but was seen with greater frequency in cats in the treated groups; it did not increase with increasing doses. Loose stool was observed in all but the 3X treatment group.

Food consumption was decreased in the 5X female cats. COMFORTIS was not associated with clinically significant changes in hematology, clinical chemistry, coagulation, or urinalysis parameters. Cats administered COMFORTIS once monthly for 6 months in the 3X and 5X dose groups demonstrated cytoplasmic vacuolation, consistent with phospholipidosis, in the liver, lung, and adrenal gland. The long term effects of phospholipidosis are unknown. The administration of COMFORTIS was not associated with any clinically significant, gross necropsy or histopathological changes.

In a well-controlled field study, COMFORTIS was administered safely in conjunction with other frequently used veterinary products, including tapeworm anthelmintics, antibiotics, and an approved heartworm preventative containing ivermectin. Hematology and clinical chemistry values were compared pre- and post-study and were unremarkable.

Storage Information:

Store at 20 to 25°C (68 to 77°F), excursions permitted between 15 to 30°C (59 to 86°F).

How Supplied:

COMFORTIS is available in three tablet sizes for use in cats: 140, 270 or 560 mg.
Each tablet size is available in color-coded packages of 6 tablets.

Comfortis™ Dogs
(spinosad)

Chewable Tablets

Caution: Federal law restricts this drug to use by or on the order of a licensed veterinarian.

Description:

COMFORTIS (spinosad) is available in five sizes of chewable flavored tablets for oral administration to dogs and puppies according to their weight. Each chewable tablet is formulated to provide a minimum spinosad dosage of 13.5 mg/lb (30 mg/kg). Spinosad is a member of the spinosyns class of insecticides, which are non-antibacterial tetracyclic macrolides. Spinosad contains two major factors, spinosyn A and spinosyn D, derived from the naturally occurring bacterium, Saccharopolyspora spinosa. Spinosyn A and spinosyn D have the chemical compositions 2-[(6-deoxy-2,3,4-tri-O-methyl-α-L-mannopyranosyl)oxy]-13-[[5-dimethylamino)-tetrahydro-6-methyl-2H-pyran-2-yl]oxy]-9-ethyl-2,3,3a,5a,5b,6,9,10,11,12,13,14,16a,16b-tetradecahydro-14-methyl-1H-as-Indaceno[3,2-d]oxacyclododecin-7,15-dione and 2-[(6-deoxy-2,3,4-tri-O-methyl-α-L-mannopyranosyl)oxy]-13-[[5-dimethylamino)-tetrahydro-6-methyl-2H-pyran-2-yl]oxy]-9-ethyl-2,3,3a,5a,5b,6,9,10,11,12,13,14,16a,16b-tetradecahydro-4,14-dimethyl-1H-as-Indaceno[3,2-d] oxacyclododecin-7,15-dione, respectively.

Indications:

COMFORTIS kills fleas and is indicated for the prevention and treatment of flea infestations (Ctenocephalides felis) for one month, on dogs and puppies 14 weeks of age and older and 5.0 pounds of body weight or greater.

Dosage and Administration:

COMFORTIS is given orally once a month, at the recommended minimum dosage of 13.5 mg/lb (30 mg/kg).

Do not use the dosing schedule below when administering COMFORTIS to cats, as it can result in an underdosage.

Dosage Schedule for Dogs:

Body Weight of Dog | Spinosad Per Tablet (mg) | Tablets Administered
5 to 10 lbs | 140 | One
10.1 to 20 lbs | 270 | One
20.1 to 40 lbs | 560 | One
40.1 to 60 lbs | 810 | One
60.1 to 120* lbs | 1620 | One
* Dogs over 120 lbs should be administered the appropriate combination of tablets.

Administer COMFORTIS with food for maximum effectiveness.

COMFORTIS is a chewable tablet and is readily consumed by dogs when offered by the owner just prior to feeding. Alternatively, COMFORTIS may be offered in food or administered like other tablet medications. COMFORTIS should be administered at monthly intervals.

If vomiting occurs within an hour of administration, redose with another full dose. If a dose is missed, administer COMFORTIS with food and resume a monthly dosing schedule.

Treatment with COMFORTIS may begin at any time of the year, preferably starting one month before fleas become active and continuing monthly through the end of flea season. In areas where fleas are common year-round, monthly treatment with COMFORTIS should continue the entire year without interruption.

To minimize the likelihood of flea reinfestation, it is important to treat all animals within a household with an approved flea protection product.

Contraindications:

There are no known contraindications for the use of COMFORTIS.

WARNINGS:

Not for human use. Keep this and all drugs out of the reach of children.

Serious adverse reactions have been reported following concomitant extra-label use of ivermectin with COMFORTIS (see Post Approval Experience).

Keep COMFORTIS in a secure location out of reach of dogs, cats, and other animals to prevent accidental ingestion or overdose.

Precautions:

COMFORTIS is for use in dogs and puppies 14 weeks of age and older (see Animal Safety).

Use with caution in breeding females (see Animal Safety). Use with caution in dogs with pre-existing epilepsy (see Adverse Reactions). The safe use of COMFORTIS in breeding males has not been evaluated.

Adverse Reactions:

In a well-controlled US field study, which included a total of 470 dogs (330 dogs treated with COMFORTIS and 140 dogs treated with an active control), no serious adverse reactions were observed with COMFORTIS. All reactions were regarded as mild and did not result in any dog being removed from the study.

Over the 90-day study period, all observations of potential adverse reactions were recorded. Reactions that occurred at an incidence > 1% within any of the 3 months of observation are presented in the following table. The most frequently reported adverse reaction in dogs in the COMFORTIS and active control groups was vomiting.

The occurrence of vomiting, most commonly within 48 hours after treatment, decreased with repeated doses of COMFORTIS.

Percentage of Dogs (%) with Adverse Reactions

 | Month 1 |  | Month 2 |  | Month 3
 | COMFORTIS Chewable Tablets (N=330) | Active Topical Control (N=139a) | COMFORTIS Chewable Tablets (N=282) | Active Topical Control (N=124) | COMFORTIS Chewable Tablets (N=260) | Active Topical Control (N=125)
Vomiting | 12.7 | 12.2 | 7.8 | 3.2 | 5.8 | 4.8
Decreased Appetite | 9.1 | 5.0 | 2.8 | 1.6 | 1.9 | 0.8
Lethargy | 7.6 | 5.0 | 3.5 | 4.0 | 1.2 | 0.8
Diarrhea | 6.7 | 5.0 | 4.3 | 0.8 | 1.2 | 0.0
Cough | 3.9 | 5.0 | 0.4 | 2.4 | 0.0 | 0.0
Polydipsia | 2.4 | 1.4 | 0.7 | 0.0 | 0.4 | 0.0
Vocalization | 1.8 | 0.0 | 0.4 | 0.0 | 0.4 | 0.0
Increased Appetite | 1.5 | 0.0 | 0.4 | 0.8 | 0.4 | 0.0
Erythema | 1.5 | 0.0 | 0.4 | 0.0 | 0.4 | 0.0
Hyperactivity | 1.2 | 1.4 | 0.0 | 0.0 | 0.4 | 0.0
Excessive Salivation | 1.2 | 0.0 | 0.4 | 0.0 | 0.0 | 0.0
a This number (n=139) is less than the total number of dogs in the safety population for the active control group (n=140) because one dog joined the study late and was only dosed at Month 3.

In US and European field studies, no dogs experienced seizures when dosed with COMFORTIS at the therapeutic dose range of 13.5-27.3 mg/lb (30-60 mg/kg), including 4 dogs with pre-existing epilepsy. Four epileptic dogs that received higher than the maximum recommended dose of 27.3 mg/lb (60 mg/kg) experienced at least one seizure within the week following the second dose of COMFORTIS, but no seizures following the first and third doses.

The cause of the seizures observed in the field studies could not be determined.

Post-Approval Experience (2023):

The following adverse events are based on post-approval adverse drug experience reporting for COMFORTIS. Not all adverse events are reported to FDA/CVM. It is not always possible to reliably estimate the adverse event frequency or establish a causal relationship to product exposure using these data.

The following adverse events reported for dogs are listed in decreasing order of reporting frequency: Vomiting, depression/lethargy, pruritus, anorexia, diarrhea, seizures, ataxia, trembling, behavioral changes, and hypersalivation.

Following concomitant extra-label use of ivermectin with COMFORTIS, some dogs have experienced the following clinical signs: Trembling/twitching, salivation/drooling, seizures, ataxia, mydriasis, blindness, and disorientation.

Post approval experience continues to support the safety of COMFORTIS when used concurrently with heartworm preventatives according to label directions.

Contact Information:

For technical assistance or to report suspected adverse drug experiences, contact Elanco US Inc. at 1-888-545-5973.

For additional information about reporting adverse drug experiences for animal drugs, contact FDA at 1-888-FDA-VETS or http://www.fda.gov/reportanimalae

Mode of Action:

The primary target of action of COMFORTIS in insects is an activation of nicotinic acetylcholine receptors (nAChRs). Spinosad does not interact with known insecticidal binding sites of other nicotinic or GABAergic insecticides such as neonicotinoids, fiproles, milbemycins, avermectins, and cyclodienes. Insects treated with spinosad show involuntary muscle contractions and tremors resulting from activation of motor neurons. Prolonged spinosad-induced hyperexcitation results in prostration, paralysis, and flea death. The selective toxicity of spinosad between insects and vertebrates may be conferred by the differential sensitivity of the insect versus vertebrate nAChRs.

Effectiveness:

In a well-controlled laboratory study, COMFORTIS began to kill fleas 30 minutes after administration and demonstrated 100% effectiveness within 4 hours. COMFORTIS kills fleas before they can lay eggs. If a severe environmental infestation exists, fleas may persist for a period of time after dose administration due to the emergence of adult fleas from pupae already in the environment. In field studies conducted in households with existing flea infestations of varying severity, flea reductions of 98.0% to 99.8% were observed over the course of 3 monthly treatments with COMFORTIS. Dogs with signs of flea allergy dermatitis showed improvement in erythema, papules, scaling, alopecia, dermatitis/pyodermatitis and pruritus as a direct result of eliminating the fleas.

Animal Safety:

COMFORTIS was tested in pure and mixed breeds of healthy dogs in well-controlled clinical and laboratory studies. No dogs were withdrawn from the field studies due to treatment-related adverse reactions.

In a dose tolerance study, COMFORTIS was administered orally to adult Beagle dogs at average doses of up to 100 mg/kg once daily for 10 consecutive days (16.7 times the maximum recommended monthly dose).

Vomiting was seen in 5 of 6 treated dogs during the first 6 days of treatment, usually within 2.5 hours of dosing. Treated females lost weight early in the treatment period, but their weights were similar to control dogs by the end of the 24-day study. COMFORTIS was not associated with any clinically significant changes in hematology, blood coagulation or urinalysis parameters; however, mild elevations in ALT occurred in all dogs treated with COMFORTIS. By day 24, ALT values had returned to near baseline levels. Phospholipidosis (vacuolation) of the lymphoid tissue was seen in all dogs treated with COMFORTIS, the long-term effects of which are unknown.

In a margin of safety study, COMFORTIS was administered orally to 6-week-old Beagle puppies at average doses of 1.5, 4.4, and 7.4 times the maximum recommended dose at 28-day intervals over a 6-month period. Vomiting was observed across all groups, including the control. Increased vomiting was observed at elevated doses, usually within 1 hour following administration. Vomiting at all doses decreased over time and stabilized when puppies were 14 weeks of age. The average daily and total weight gains of treated dogs were smaller than control dogs and were dose dependent. COMFORTIS was not associated with clinically significant changes in hematology, clinical chemistry, coagulation or urinalysis parameters. Phospholipidosis (vacuolation) of the lymphoid tissue was seen in some dogs in the 4.4X group and all dogs in the 7.4X group. The long term effects of phospholipidosis are unknown. Treatment with COMFORTIS was not associated with any other clinically significant adverse clinical observations, gross necropsy or histopathological changes.

In a reproductive safety study, COMFORTIS was administered orally to female Beagles at 1.3 and 4.4 times the maximum recommended therapeutic dose every 28 days prior to mating, during gestation, and during a six-week lactation period. No treatment-related adverse effects were noted for conception rates in the dams, or for mortality, body temperature, necropsy, or histopathology findings for the dams or puppies. One dam from each treatment group experienced early pregnancy loss and one additional high dose dam aborted late term. The treated dams experienced more vomiting, especially at one hour post-dose, than the control dams. Puppies from dams treated at 1.3 times the maximum recommended therapeutic dose had lower body weights than puppies from control dams. Although puppy mortality between treated and control dams was not different, the puppies from the treated dams experienced more lethargy (4.4X group only), dehydration, weakness and felt cold to the touch (4.4X group only) than puppies from control dams.

A pilot study without a control group was conducted to analyze milk from three lactating dogs treated with an experimental formulation of spinosad at 1.5 times the maximum recommended dose administered at day 28 of gestation and 24 hours prior to parturition. The data demonstrated that spinosyns were excreted in the milk of these dogs. Mortality and morbidity were greatest in puppies from the dam with the highest spinosyns level in milk. The spinosad milk: reference plasma exposure ratio calculated from this study ranged from 2.2 to 3.5.

In well-controlled field studies, COMFORTIS was administered safely in conjunction with other frequently used veterinary products, such as vaccines, anthelmintics, antibiotics, steroids, flea and tick control products, anesthetics, NSAIDs, antihistamines, alternative/herbal remedies, shampoos, and prescription diets. Changes in hematology, clinical chemistry and urinalysis values were compared pre- and post-study and were unremarkable.

Storage Information:

Store at 20-25°C (68 -77°F), excursions permitted between 15 to 30°C (59 to 86°F).

How Supplied:

COMFORTIS is available in five tablet sizes for use in dogs: 140, 270, 560, 810 or 1620 mg.
Each tablet size is available in color-coded packages of 6 tablets.

Approved by FDA under NADA # 141-277

Manufactured for:
Elanco US Inc.
Greenfield, IN 46140
www.comfortis.com

Comfortis, Elanco and the diagonal bar logo are trademarks of
Elanco or its affiliates.

© 2024 Elanco or its affiliates

CA4222, CA4223, CA4224, CA4225, CA4227

Elanco™

Revised: June 2024

Information for Cat and Dog Owners

COMFORTIS™ Cats
(spinosad)

Chewable Tablets

Your veterinarian has chosen to prescribe COMFORTIS to meet your flea treatment and prevention needs. Controlling fleas is important to the health of your cat. Please read this leaflet, which describes the proper use of COMFORTIS to treat and prevent flea infestations. If you have any questions about this information, please consult your veterinarian. Additional information can be found at www.comfortis.com.

What is COMFORTIS?

COMFORTIS is a chewable, flavored tablet that you give to your cat to kill fleas and prevent flea infestations for one month. COMFORTIS is for monthly use in cats and kittens 14 weeks of age or older and 4.1 pounds of body weight or greater.

Why has my veterinarian prescribed COMFORTIS?

Your veterinarian has provided this medication to either prevent a flea infestation or to treat an existing flea infestation on your cat.

What should I discuss with my veterinarian regarding COMFORTIS for my cat?

Your veterinarian is your cat’s healthcare expert and can make the best recommendation for medications for your cat. This includes the prevention and treatment of parasites such as fleas that may cause conditions that include flea allergy dermatitis, anemia, and other flea-related problems.

Key points of your discussion may include the following:

- Treatment with COMFORTIS may begin at any time of the year, preferably starting one month before fleas become active and continuing through the end of flea season. In areas where fleas may occur year-round, monthly treatment with COMFORTIS should continue the entire year without interruption.
- If a dose is missed, administer COMFORTIS with food and resume a monthly dosing schedule.
- To minimize the likelihood of flea reinfestation, it is important to treat all animals within a household with an approved flea protection product.
- COMFORTIS is not for use in humans. Like all medications, keep COMFORTIS out of reach of children.
- Make sure your veterinarian is aware of all medications, including over-the-counter (OTC) medications, that you are giving to your cat.
- Keep COMFORTIS in a secure location out of reach of dogs, cats, and other animals to prevent accidental ingestion or overdose.

How should I give COMFORTIS to my cat?

Give COMFORTIS with food for maximum effectiveness. COMFORTIS is a chewable tablet that can be consumed by cats when offered just prior to or just after feeding. Alternatively, COMFORTIS may be offered in food or administered like other tablet medications. Give COMFORTIS to your cat once a month.

What if I give more than the prescribed amount of COMFORTIS to my cat?

In pre-approval clinical studies, the most severe adverse reaction observed at elevated dose rates was increased vomiting and loose stool. In the event of possible overdose, contact your veterinarian, who is the healthcare expert for your cat.

Should I restrict either my cat's activity or contact with my cat after the tablet is consumed?

Since COMFORTIS is an oral formulation, you may maintain normal activities and interactions with your cat.

How quickly will COMFORTIS kill fleas?

In a laboratory study, COMFORTIS started to kill fleas within 30 minutes and killed 100% of the fleas within 24 hours. COMFORTIS kills fleas before they can lay eggs.

Does seeing fleas on my cat mean that the treatment is not working?

COMFORTIS kills fleas before they can lay eggs when used monthly according to the label directions. Remember that all animals in the household should be treated with an approved flea product to help control the flea population. Female fleas that are living on animals produce eggs that fall from the animal into their surroundings. These eggs hatch within a week; larvae then emerge and spin cocoons to become pupae. The entire life cycle can be completed in as little as 3 weeks, with new adult fleas emerging from the pupae to jump onto your cat. Because each female flea can lay up to 50 eggs per day, there is potential for a large build-up of eggs, larvae and pupae, resulting in a constant supply of new adults emerging in the cat’s environment.

Regardless of the product used to kill the fleas, the cat can continue to be exposed to the fleas that live in the environment. If these fleas jump onto the cat, they will be killed by COMFORTIS. If you see fleas on your cat within a month after your cat receives COMFORTIS, it is most likely that these are new fleas that have recently emerged from pupae and jumped onto the cat. These new fleas will be killed before they can produce eggs that contaminate the environment.

Is it safe to give my cat COMFORTIS?

COMFORTIS has been demonstrated to be safe in cats when used according to label directions. Safety was shown in cats and kittens 14 weeks of age and older, in multiple laboratory studies and a field study in household cats. The safe use of COMFORTIS in breeding, pregnant, or lactating cats has not been evaluated.

What side effects might occur with COMFORTIS?

Side effects may occur after administration of COMFORTIS. In some cases, cats vomited after receiving COMFORTIS. If vomiting occurs within one hour of administration, redose with another full dose.

Additional adverse reactions observed in clinical studies were lethargy, decreased appetite, weight loss, and diarrhea. Since the introduction of COMFORTIS, additional side effects reported are behavioral changes, itching, incoordination, hyperactivity, excessive salivation, panting, vocalization, difficulty breathing, twitching, and seizures.

In some cases, death was reported. Some of these reports involved cats with heart disease, including cats with previously undiagnosed heart disease.

Can other medications be given while my cat is taking COMFORTIS?

Yes, COMFORTIS has been given safely with a wide variety of products and medications. Your veterinarian should be made aware of all medications, including over-the-counter (OTC) medications, that you are giving to your cat. For heartworm prevention, use products that are specifically prescribed by your veterinarian.

How should COMFORTIS be stored?

Store at 68 to 77°F (20 to 25°C). Temporary periods of time outside of this range between 59 to 86°F (15 to 30°C) are permitted.

If you have questions regarding the use of this product, consult your veterinarian, your cat’s healthcare expert. Additional information can be found at www.comfortis.com.

For technical assistance or to report suspected adverse drug events, contact Elanco US Inc. at 1-888-545-5973. For additional information about adverse drug experience reporting for animal drugs, contact FDA at 1-888-FDA-VETS or http://www.fda.gov/reportanimalae

COMFORTIS™ Dogs
(spinosad)

Chewable Tablets

Your veterinarian has chosen to prescribe COMFORTIS to meet your flea treatment and prevention needs. Controlling fleas is very important to the health of your dog. Please read this leaflet, which describes the use of COMFORTIS to treat and prevent flea infestations. If you have any questions about this information, please consult your veterinarian. Additional information can be found at www.comfortis.com.

What is COMFORTIS?

COMFORTIS is a chewable, flavored tablet that you give to your dog to kill fleas and prevent flea infestations for one month. COMFORTIS is for monthly use in dogs and puppies 14 weeks of age or older and 5.0 pounds of body weight or greater.

Why has my veterinarian prescribed COMFORTIS?

Your veterinarian has provided this medication to either prevent a flea infestation or to treat an existing infestation on your dog.

What should I discuss with my veterinarian regarding COMFORTIS for my dog?

Your veterinarian is your dog’s healthcare expert and can make the best recommendation for medications for your dog. This includes the prevention and treatment of parasites such as fleas that may cause conditions that include flea allergy dermatitis, anemia, and other flea-related problems.

Key points of your discussion may include the following:

- Treatment with COMFORTIS may begin at any time of the year, preferably starting one month before fleas become active and continuing through the end of flea season. In areas where fleas may occur year-round, monthly treatment with COMFORTIS should continue the entire year without interruption.
- If a dose is missed, administer COMFORTIS with food and resume a monthly dosing schedule.
- To minimize the likelihood of flea reinfestation, it is important to treat all animals within a household with an approved flea protection product.
- COMFORTIS is not for use in humans. Like all medications, keep COMFORTIS out of reach of children.
- Keep COMFORTIS in a secure location out of reach of dogs, cats, and other animals to prevent accidental ingestion or overdose.
- Make sure your veterinarian is aware of all medications, including over the counter (OTC) medications, that you are giving to your dog.

How should I give COMFORTIS to my dog?

Give COMFORTIS with food for maximum effectiveness.

COMFORTIS is a chewable tablet and is readily consumed by dogs when offered by the owner just prior to feeding. Alternatively, COMFORTIS may be offered in food or administered like other tablet medications.

Give COMFORTIS to your dog once a month.

What if I give more than the prescribed amount of COMFORTIS to my dog?

In pre-approval clinical studies, the most severe adverse reaction observed at elevated dose rates was increased vomiting. In the event of possible overdose, contact your veterinarian, who is the healthcare expert for your dog.

Should I restrict either my dog's activity or contact with my dog after the tablet is consumed?

Since COMFORTIS is an oral formulation, you may maintain normal activities and interactions with your dog.

How quickly will COMFORTIS kill fleas?

In a laboratory study, COMFORTIS started to kill fleas within 30 minutes and killed 100% of the fleas within 4 hours. COMFORTIS kills fleas before they can lay eggs.

Does seeing fleas on my dog mean that the flea treatment is not working?

COMFORTIS kills fleas before they can lay eggs when used monthly according to the label directions. Remember that all animals in the household should be treated with an approved flea product to help control the flea population.

Female fleas that are living on animals produce eggs that fall from the animal into their surroundings. These eggs hatch within a week; larvae then emerge and spin cocoons to become pupae. The entire life cycle can be completed in as little as 3 weeks, with new adult fleas emerging from the pupae to jump onto your dog. Because each female flea can lay up to 50 eggs per day there is potential for a large build-up of eggs, larvae and pupae, resulting in a constant supply of new adults emerging in the dog’s environment.

Regardless of the product used to kill the fleas, the dog can continue to be exposed to the fleas that live in the environment. When these fleas jump onto the dog, they will be quickly killed by COMFORTIS.

If you see fleas on your dog within a month after your dog receives COMFORTIS, it is most likely that these are new fleas that have very recently emerged from pupae and jumped onto the dog. These new fleas will quickly be killed before they can produce eggs that contaminate the environment.

Is it safe to give my dog COMFORTIS?

COMFORTIS has been demonstrated to be safe in pure and mixed breeds of healthy dogs when used according to label directions. Safety was shown in puppies 14 weeks of age and older and adult dogs in both laboratory studies and clinical field studies. You should discuss the use of COMFORTIS with your veterinarian prior to use if your dog has a history of epilepsy (seizures).

Is it safe to give my breeding dogs COMFORTIS?

Use with caution in breeding females. You should discuss the use of COMFORTIS with your veterinarian prior to use in breeding females. Safe use of COMFORTIS in male dogs intended for breeding has not been evaluated.

What side effects might occur with COMFORTIS?

Side effects may occur after administration of COMFORTIS. In some cases, dogs vomited after receiving COMFORTIS. If vomiting occurs within one hour of administration, redose with another full dose. During clinical studies, no severe or prolonged vomiting occurred. Additional adverse reactions observed in the clinical studies were decreased appetite, lethargy or decreased activity, diarrhea, cough, increased thirst, vocalization, increased appetite, redness of the skin, hyperactivity, and excessive salivation. These reactions were regarded as mild and did not result in any dog being removed from the studies. Since the introduction of COMFORTIS, additional side effects reported are itching, seizures, incoordination, trembling, and behavioral changes.

Can other medications be given while my dog is taking COMFORTIS?

Yes, COMFORTIS has been given safely with a wide variety of products and medications. Your veterinarian should be made aware of all products that you administered and/or intend to administer to your dog. For heartworm prevention, use products that are specifically prescribed by your veterinarian.

How should COMFORTIS be stored?

Store at 68-77°F (20-25°C). Temporary periods of time outside of this range between 59-86°F (15-30°C) are permitted.

If you have questions regarding the use of this product, consult your veterinarian, your dog’s healthcare expert. Additional information can be found at www.comfortis.com.

For technical assistance or to report suspected adverse drug events, contact Elanco US Inc. at 1-888-545-5973.

For additional information about adverse drug experience reporting for animal drugs, contact FDA at 1-888-FDA-VETS or http://www.fda.gov/reportanimalae

Elanco™

Revised: June 2024

Principal Display Panel - 140 mg Carton Label

FOR CATS
4.1-6 lbs

FOR DOGS
5-10 lbs

KILLS FLEAS
FAST ACTING
ONCE A MONTH

6 CHEWABLE
TABLETS
140 mg

Comfortis™
(spinosad)

CAUTION: Federal (USA) law restricts this drug to use by or on the order of a licensed veterinarian.

KILLS FLEAS AND PREVENTS INFESTATIONS

For use in dogs and puppies 14 weeks of age and older.

For use in cats and kittens 14 weeks of age and older.

Starts killing fleas
in 30 mins.

Kills fleas before
they can lay eggs

Give with
a meal

Approved by FDA under NADA # 141-277

Elanco™

Principal Display Panel - 270 mg Carton Label

FOR CATS
6.1-12 lbs

FOR DOGS
10.1-20 lbs

KILLS FLEAS
FAST ACTING
ONCE A MONTH

6 CHEWABLE
TABLETS
270 mg

Comfortis™
(spinosad)

CAUTION: Federal (USA) law restricts this drug to use by or on the order of a licensed veterinarian.

KILLS FLEAS AND PREVENTS INFESTATIONS

For use in dogs and puppies 14 weeks of age and older.

For use in cats and kittens 14 weeks of age and older.

Starts killing fleas
in 30 mins.

Kills fleas before
they can lay eggs

Give with
a meal

Approved by FDA under NADA # 141-277

Elanco™

Principal Display Panel - 560 mg Carton Label

FOR CATS
12.1-24 lbs

FOR DOGS
20.1-40 lbs

KILLS FLEAS
FAST ACTING
ONCE A MONTH

6 CHEWABLE
TABLETS
560 mg

Comfortis™
(spinosad)

CAUTION: Federal (USA) law restricts this drug to use by or on the order of a licensed veterinarian.

KILLS FLEAS AND PREVENTS INFESTATIONS

For use in dogs and puppies 14 weeks of age and older.

For use in cats and kittens 14 weeks of age and older.

Starts killing fleas
in 30 mins.

Kills fleas before
they can lay eggs

Give with
a meal

Approved by FDA under NADA # 141-277

Elanco™

Principal Display Panel - 810 mg Carton Label

FOR DOGS
40.1-60 lbs

KILLS FLEAS
FAST ACTING
ONCE A MONTH

6 CHEWABLE
TABLETS
810 mg

Comfortis™
(spinosad)

CAUTION: Federal (USA) law restricts this drug to use by or on the order of a licensed veterinarian.

KILLS FLEAS AND PREVENTS INFESTATIONS

For use in dogs and puppies 14 weeks of age and older.

Starts killing fleas
in 30 mins.

Kills fleas before
they can lay eggs

Give with
a meal

Approved by FDA under NADA # 141-277

Elanco™

Principal Display Panel - 1620 mg Carton Label

FOR DOGS
60.1-120 lbs

KILLS FLEAS
FAST ACTING
ONCE A MONTH

6 CHEWABLE
TABLETS
1620 mg

Comfortis™
(spinosad)

CAUTION: Federal (USA) law restricts this drug to use by or on the order of a licensed veterinarian.

KILLS FLEAS AND PREVENTS INFESTATIONS

For use in dogs and puppies 14 weeks of age and older.

Starts killing fleas
in 30 mins.

Kills fleas before
they can lay eggs

Give with
a meal

Approved by FDA under # NADA 141-277

Elanco™